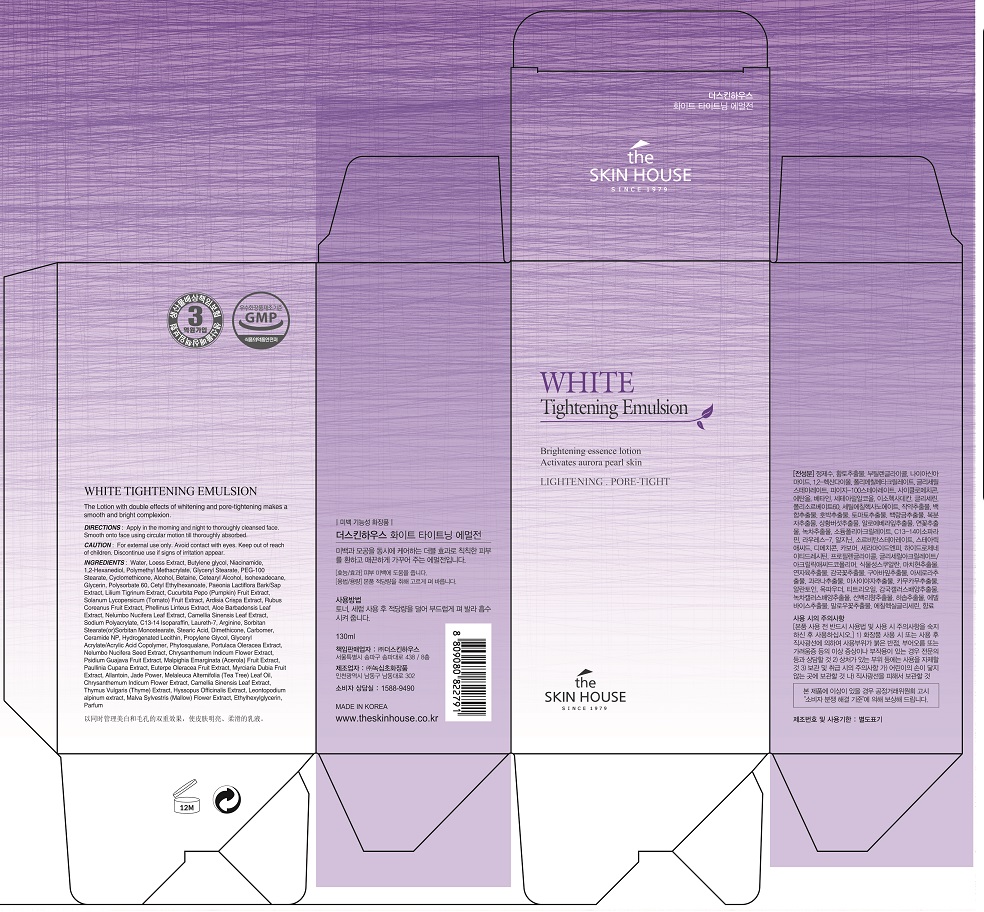 DRUG LABEL: THE SKINHOUSE WHITE TIGHTENINGEMULSION
NDC: 73590-0002 | Form: EMULSION
Manufacturer: NOKSIBCHO cosmetic Co., Ltd.
Category: otc | Type: HUMAN OTC DRUG LABEL
Date: 20200127

ACTIVE INGREDIENTS: NIACINAMIDE 2 g/100 mL
INACTIVE INGREDIENTS: WATER; BUTYLENE GLYCOL

Drug Facts

ACTIVE INGREDIENT

Niacinamide, HamamelisVirginiana (Witch Hazel) Extract, PaeoniaLactiflora Bark/ Sap Extract, LiliumTigrinum Extract, ArdisiaCrispa Extract, Phellinus Linteus Extract, Camellia Sinensis Leaf Extract

INACTIVE INGREDIENT

Water
Loess Extract
Butylene glycol
Niacinamide
1,2-Hexanediol
Polymethyl Methacrylate
Glyceryl Stearate
PEG-100 Stearate
Cyclomethicone
Alcohol
Betaine
Cetearyl Alcohol
Isohexadecane
Glycerin
Polysorbate 60
Cetyl Ethylhexanoate
Paeonia Lactiflora Bark/Sap Extract
Lilium Tigrinum Extract
Cucurbita Pepo (Pumpkin) Fruit Extract
Solanum Lycopersicum (Tomato) Fruit Extract
Ardisia Crispa Extract
Rubus Coreanus Fruit Extract
Phellinus Linteus Extract
Aloe Barbadensis Leaf Extract
Nelumbo Nucifera Leaf Extract
Camellia Sinensis Leaf Extract
Sodium Polyacrylate
C13-14 Isoparaffin
Laureth-7
Arginine
Sorbitan Stearate(or)Sorbitan Monostearate
Stearic Acid
Dimethicone
Carbomer
Ceramide NP
Hydrogenated Lecithin
Glycerin
Propylene Glycol
Alcohol
Water
Glyceryl Acrylate/Acrylic Acid Copolymer
Propylene Glycol
Phytosqualane
Portulaca Oleracea Extract
Paeonia Lactiflora Bark/Sap Extract
Nelumbo Nucifera Seed Extract
Chrysanthemum Indicum Flower Extract
Psidium Guajava Fruit Extract
Malpighia Emarginata (Acerola) Fruit Extract
Paullinia Cupana Extract
Euterpe Oleracea Fruit Extract
Myrciaria Dubia Fruit Extract
Euterpe Oleracea Fruit Extract
Allantoin
Jade Power
Melaleuca Alternifolia (Tea Tree) Leaf Oil
Chrysanthemum Indicum Flower Extract
Camellia Sinensis Leaf Extract
Thymus Vulgaris (Thyme) Extract
Hyssopus Officinalis Extract
Leontopodium alpinum extract
Malva Sylvestris (Mallow) Flower Extract
Ethylhexylglycerin
Parfum

PURPOSE

For those who want whitening products but not dry one.

This emulsion does not only help pore care, but also help whitening effect.

It controls the level between oil and moisture so that the pore is tightened and the skin tone becomes bright and even. Also the moisture supply effect will give a fresh feeling as well as moist feeling. It is a soft type of emulsion so it can make the shiny skin like ceramic

keep out of reach of the children

INDICATIONS AND USAGE

After cleansing, use toner to smooth the skin texture.

Apply an adequate amount of the emulsion to the face, and spread it softly.

Pat your face to be absorbed completely.

WARNINGS

For external use only
When using this product

■ if the following symptoms occurs after use, stop use and consult with a skin specialist

red specks, swelling, itching

■ don’t use on the part where there is injury, eczema, or dermatitis

Keep out of reach of children

■ if swallowed, get medical help or contact a person control center immediately

DOSAGE AND ADMINISTRATION

for external use only